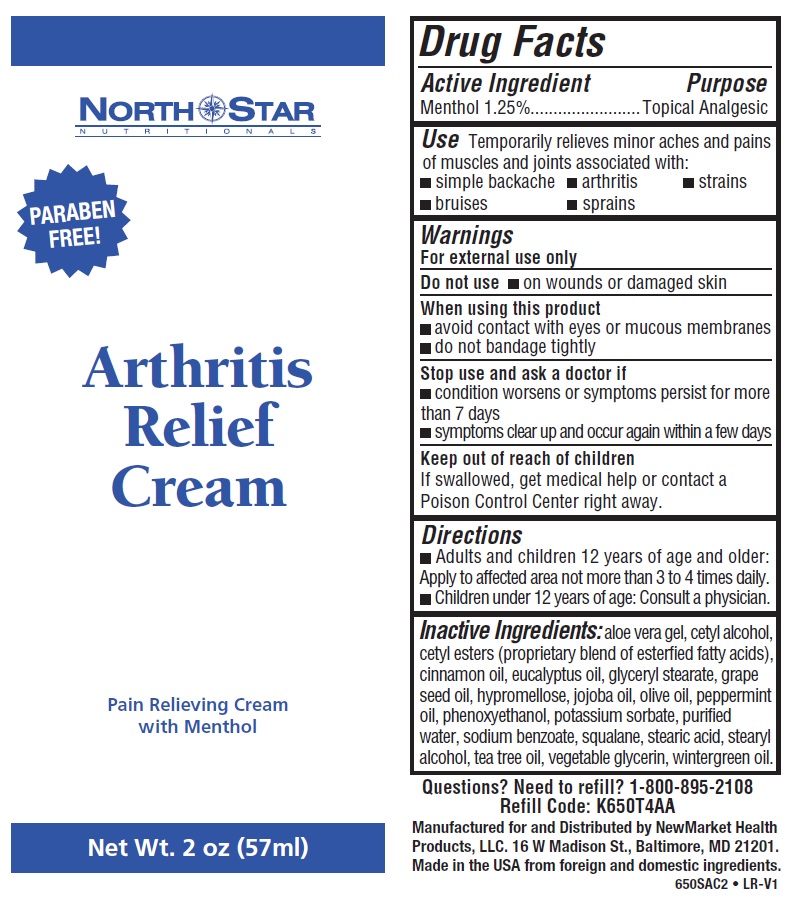 DRUG LABEL: Arthritis Relief Cream
NDC: 50972-275 | Form: CREAM
Manufacturer: NewMarket Health Products LLC
Category: otc | Type: HUMAN OTC DRUG LABEL
Date: 20210120

ACTIVE INGREDIENTS: MENTHOL, UNSPECIFIED FORM 12.5 mg/1 mL
INACTIVE INGREDIENTS: ALOE VERA LEAF; CETYL ALCOHOL; CETYL ESTERS WAX; CINNAMON OIL; EUCALYPTUS OIL; GLYCERYL MONOSTEARATE; GRAPE SEED OIL; HYPROMELLOSE, UNSPECIFIED; JOJOBA OIL; OLIVE OIL; PEPPERMINT OIL; PHENOXYETHANOL; POTASSIUM SORBATE; WATER; SODIUM BENZOATE; SQUALANE; STEARIC ACID; STEARYL ALCOHOL; TEA TREE OIL; GLYCERIN; METHYL SALICYLATE

Arthritis Relief Cream

Active Ingredient section

Menthol, Unspecified Form 1.25%

Purpose

Topical Analgesic

Uses

Temporarily relieves minor aches and pains of muscles and joints associated with:
• Simple backache
• Arthritis
• Strains
• Bruises
• Sprains

Warnings

For external use only.

Do not use

• On wounds or damaged skin

When using this product
• Avoid contact with eyes or mucous membranes
• Do not bandage tightly

Stop use and ask a doctor if
• Condition worsens or symptoms persist for more than 7 days
• Symptoms clear up and occur again within a few days

Keep out of reach of children.

If swallowed, get medical help or contact a Poison Control Center right away.

Directions

• Adults and children 12 years of age and older: Apply to affected area not more than 3 to 4 times daily.
• Children under 12 years of age: Consult a physician.

Other Information.

Questions? Need to refill? 1-800-895-2108

Inactive Ingredients

Aloe Vera Gel, Cetyl Alcohol, Cetyl Esters (proprietary blend of esterified fatty acids), Cinnamon Oil, Eucalyptus Oil, Glyceryl Stearate, Grape Seed Oil, Hypromellose, Jojoba Oil, Olive Oil, Peppermint Oil, Phenoxyethanol, Potassium Sorbate, Purified Water, Sodium Benzoate, Squalane, Stearic Acid, Stearyl Alcohol, Tea Tree Oil, Vegetable Glycerin, Wintergreen Oil.